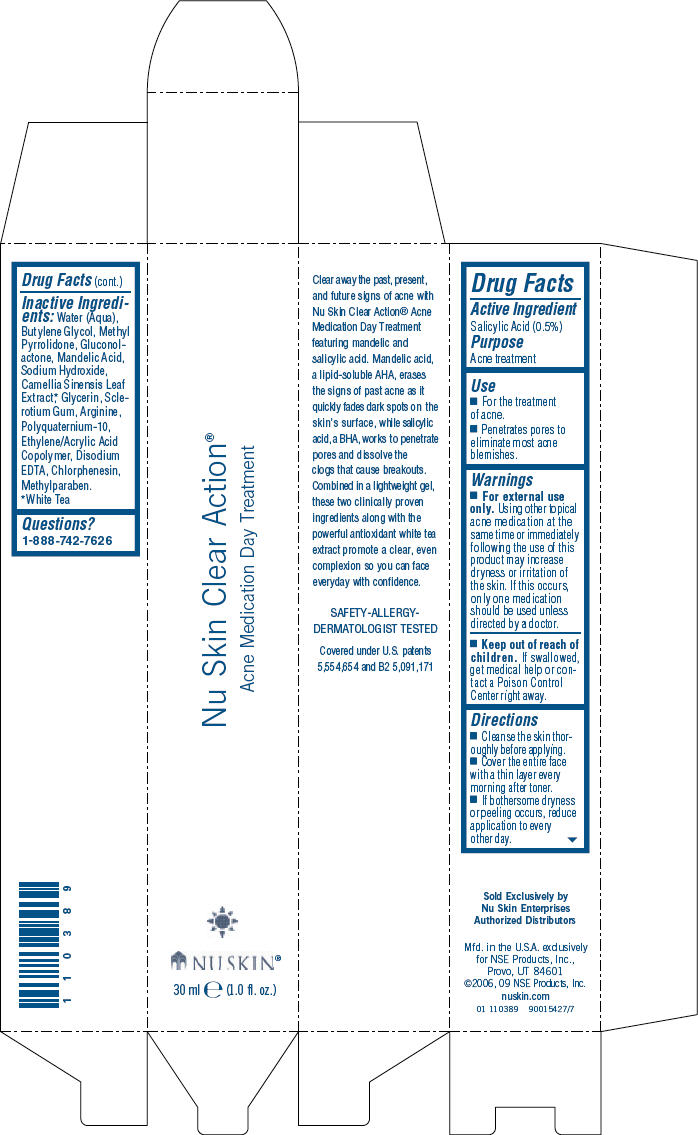 DRUG LABEL: Nu Skin
NDC: 62839-1038 | Form: GEL
Manufacturer: NSE Products, Inc.
Category: otc | Type: HUMAN OTC DRUG LABEL
Date: 20241230

ACTIVE INGREDIENTS: Salicylic Acid 5 g/1000 mL
INACTIVE INGREDIENTS: Water; Butylene Glycol; METHYLPYRROLIDONE; Gluconolactone; Mandelic Acid; Sodium Hydroxide; Green Tea Leaf; Glycerin; Arginine; Edetate Disodium; Chlorphenesin; Methylparaben

Nu Skin Clear Action®
Acne Medication Day Treatment

Drug Facts

Active Ingredient

Salicylic Acid (0.5%)

Purpose

Acne treatment

Use

- For the treatment of acne.
- Penetrates pores to eliminate most acne blemishes.

Warnings

- For external use only.

WHEN USING

Using other topical acne medication at the same time or immediately following the use of this product may increase dryness or irritation of the skin. If this occurs, only one medication should be used unless directed by a doctor.

- Keep out of reach of children. If swallowed, get medical help or contact a Poison Control Center right away.

Directions

- Cleanse the skin thoroughly before applying.
- Cover the entire face with a thin layer every morning after toner.
- If bothersome dryness or peeling occurs, reduce application to every other day.

Inactive Ingredients

Water (Aqua), Butylene Glycol, Methyl Pyrrolidone, Gluconolactone, Mandelic Acid, Sodium Hydroxide, Camellia Sinensis Leaf Extract, [White Tea] Glycerin, Sclerotium Gum, Arginine, Polyquaternium-10, Ethylene/Acrylic Acid Copolymer, Disodium EDTA, Chlorphenesin, Methylparaben.

Questions?

1-888-742-7626

PRINCIPAL DISPLAY PANEL - 30 ml Carton

Nu Skin Clear Action®

Acne Medication Day Treatment

NU SKIN ®

30 ml e (1.0 fl. oz.)